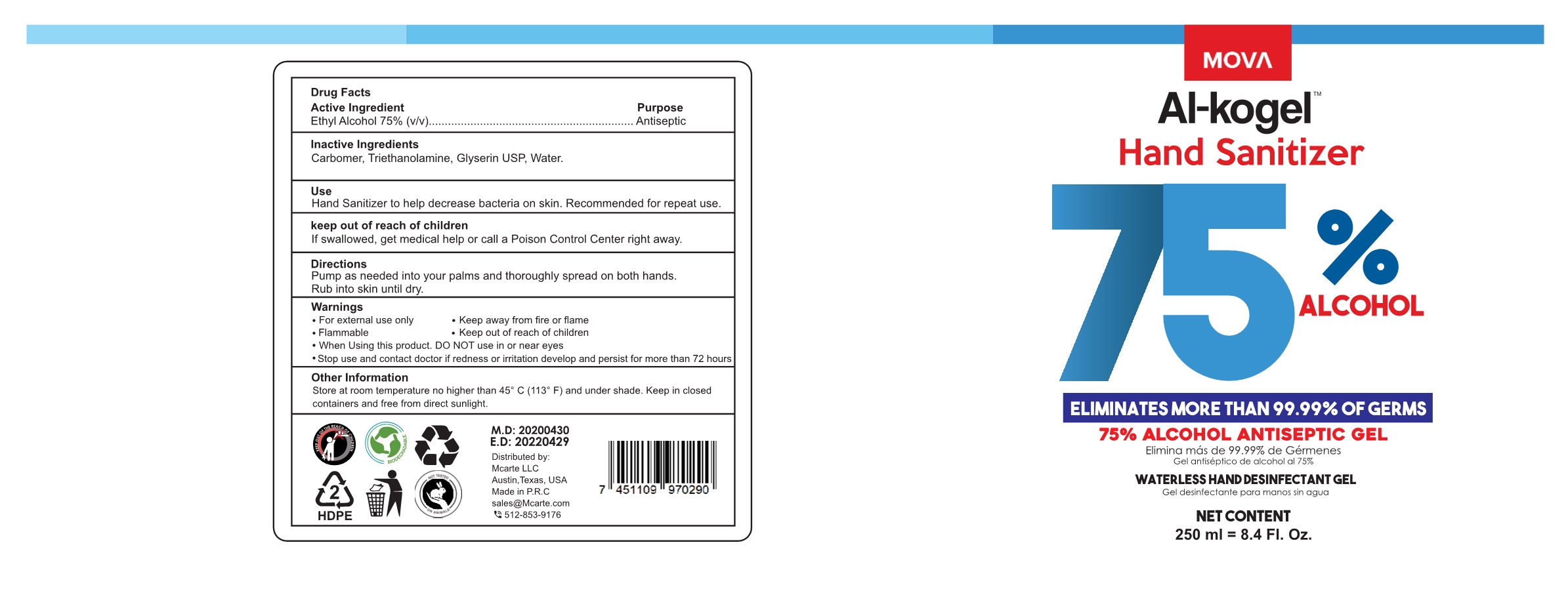 DRUG LABEL: Al kogel Hand Sanitizer
NDC: 52989-006 | Form: GEL
Manufacturer: Taizhou Yadai Daily-Use Co., Ltd.
Category: otc | Type: HUMAN OTC DRUG LABEL
Date: 20200803

ACTIVE INGREDIENTS: ALCOHOL 75 mL/100 mL
INACTIVE INGREDIENTS: GLYCERIN; CARBOMER 940; TROLAMINE; WATER

52989-006 Al-kogel

Active Ingredient(s)

Ethyl Alcohol 75% v/v

Purpose

Antiseptic

Use

Hand sanitizer to help decrease bacteria on the skin

Recommended for repeated use

Warnings

For external use only. Flammable. Keep away from fire or flame

When using this product, do not use in or near eyes

Stop use and ask a doctor if redness or irritation develop and last for more than 72 hours

Keep out of reach of children. If swallowed, get medical help or call a Poison Control Center right away.

Directions

- Pump as needed into your palms and thoroughly spead on both hands. Rub into skin until dry.

Other Information

Store at room temperature no higher than 45 C (113 F) and under shade. Keep in closed containers and free from direct sunlight.

Inactive Ingredients

Carbomer, Triethanolamine, Glycerin, Water